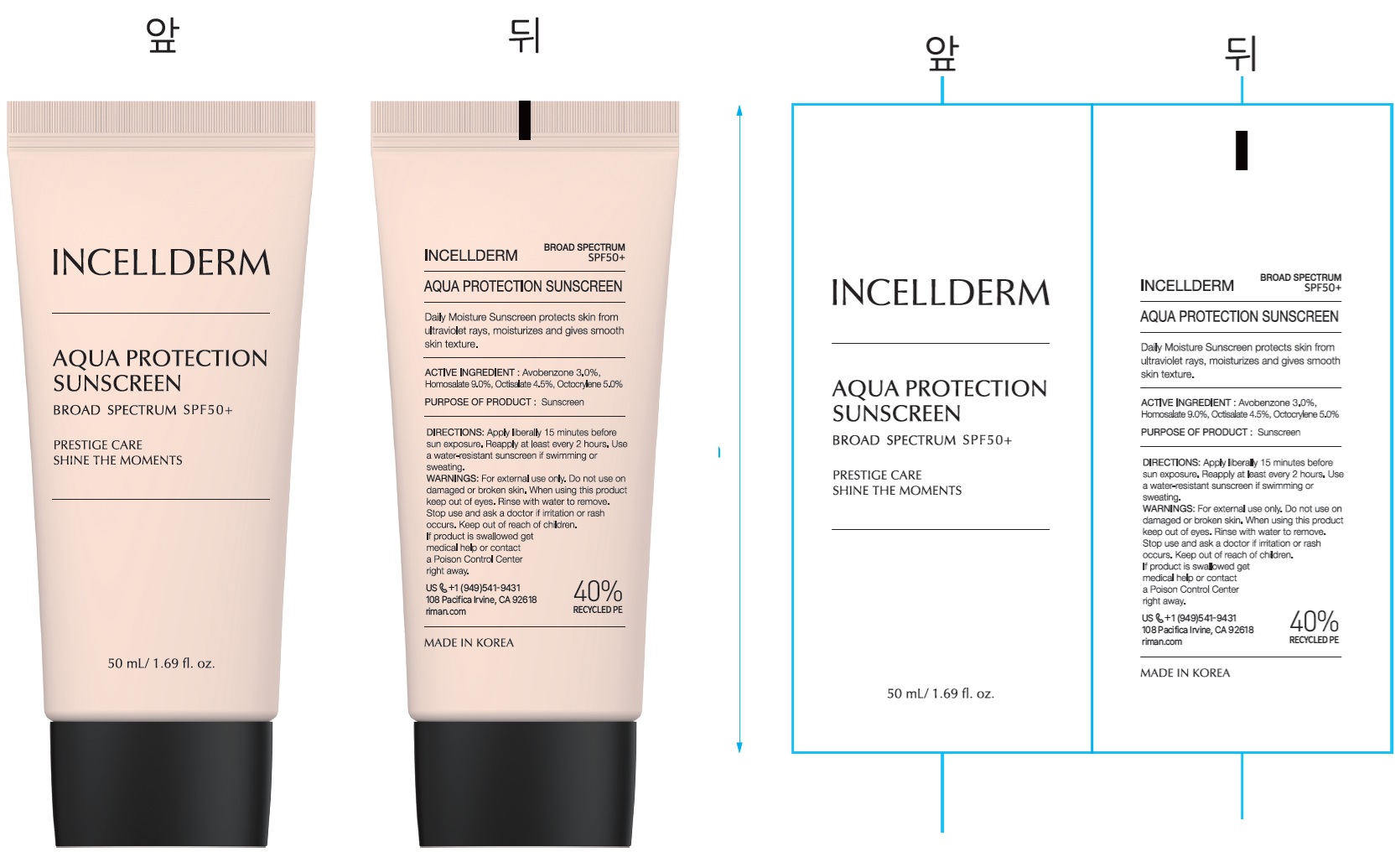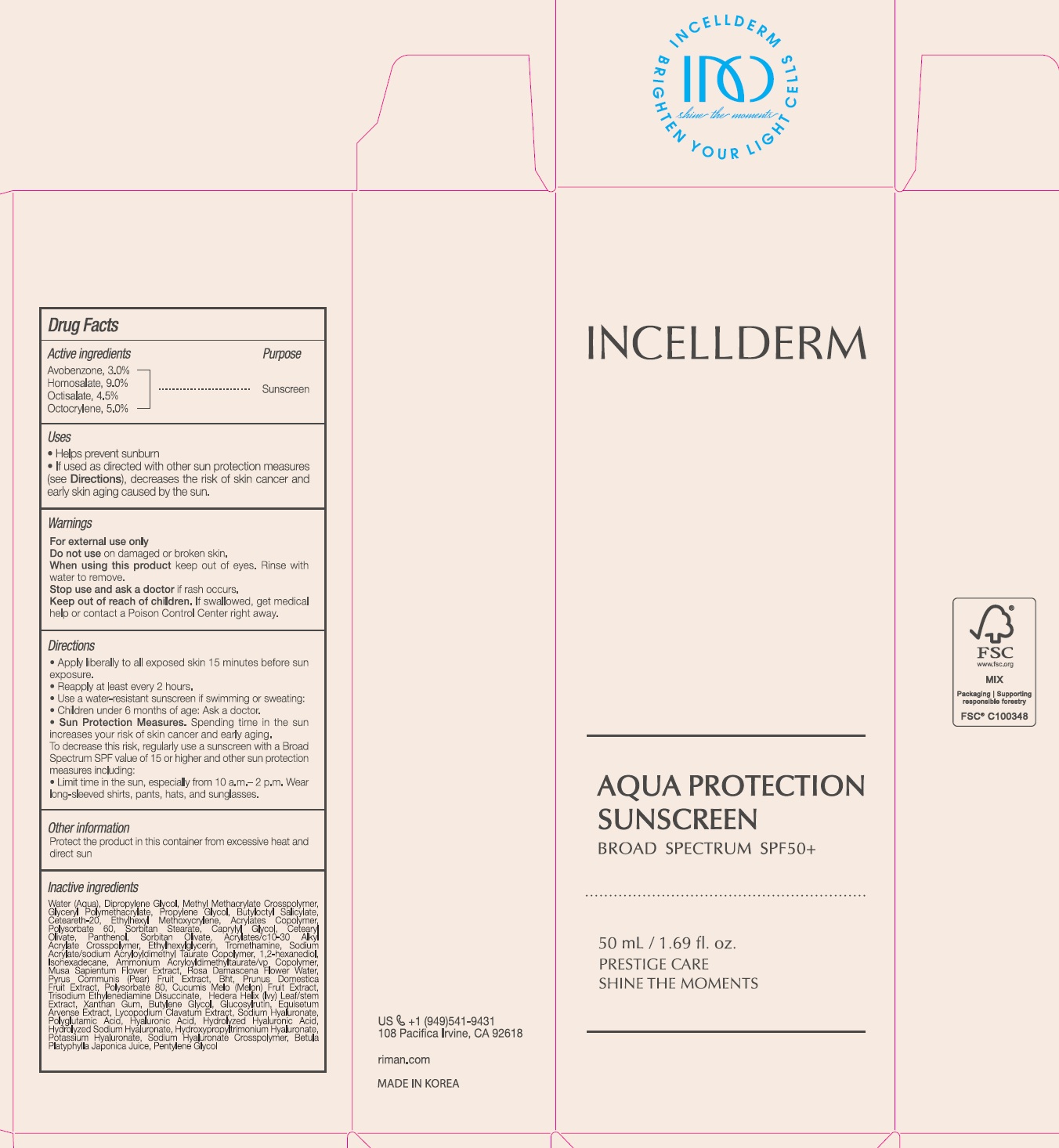 DRUG LABEL: Aqua protection Sunscreen Broad Spectrum SPF50
NDC: 14268-122 | Form: LOTION
Manufacturer: ENGLEWOOD LAB, INC.
Category: otc | Type: HUMAN OTC DRUG LABEL
Date: 20260123

ACTIVE INGREDIENTS: AVOBENZONE 30 mg/1 mL; HOMOSALATE 90 mg/1 mL; OCTISALATE 45 mg/1 mL; OCTOCRYLENE 50 mg/1 mL
INACTIVE INGREDIENTS: WATER; DIPROPYLENE GLYCOL; PROPYLENE GLYCOL; BUTYLOCTYL SALICYLATE; POLYOXYL 20 CETOSTEARYL ETHER; ETHYLHEXYL METHOXYCRYLENE; POLYSORBATE 60; SORBITAN STEARATE; CAPRYLYL GLYCOL; CETEARYL OLIVATE; PANTHENOL; SORBITAN OLIVATE; ETHYLHEXYLGLYCERIN; TROMETHAMINE; 1,2-HEXANEDIOL; ISOHEXADECANE; AMMONIUM ACRYLOYLDIMETHYLTAURATE/VP COPOLYMER; ROSA X DAMASCENA FLOWER OIL; PEAR; BUTYLATED HYDROXYTOLUENE; PLUM; POLYSORBATE 80; MUSKMELON; TRISODIUM ETHYLENEDIAMINE DISUCCINATE; HEDERA HELIX TOP; XANTHAN GUM; BUTYLENE GLYCOL; EQUISETUM ARVENSE BRANCH; HYALURONATE SODIUM; HYALURONIC ACID; BETULA PENDULA SUBSP. MANDSHURICA RESIN; PENTYLENE GLYCOL

Aqua protection Sunscreen Broad Spectrum SPF50+

Active Ingredients

Avobenzone, 3.0%

Homosalate 9.0%

Octisalate 4.5%

Octocrylene, 5.0%

Purpose

Sunscreen

Uses

- Helps prevent sunburn
- If used as directed with other sun protection measures (see), decreases the risk of skin cancer and early skin aging caused by the sun. Directions

Warnings

For external use only

Do not use

on damaged or broken skin.

When using this product

keep out of eyes. Rinse with water to remove.

Stop use and ask a doctor

ir rash occurs.

Keep out of reach of children.

If swallowed, get medical help or contact a Poison Control Center right away.

Directions

- Apply liberally to all exposed skin 15 minutes before sun exposure.
- Reapply at least evey 2 hours.
- Use a water-resistant sunscreen if swimming or sweating:
- Children under 6 months of age: Ask a doctor.
- Spending time in the sun increases your risk of skin cancer and early aging. To decrease this risk, regularly use a sunscreen with a Broad Spectrum SPF value of 15 or higher and other sun protection measures including: Sun Protection Measures.
- Limit time in the sun, especially from 10 a.m. - 2 p.m. Wear long-sleeved shirts, pants, hats, and sunglasses.

Othe information

Protect the product in this container from excessive heat and direct sun

Inactive ingredients

Water (Aqua), Dipropylene Glycol, Methyl Methacrylate Crosspolymer, Glyceryl Polymethacrylate, Propylene Glycol, Butyloctyl Salicylate, Ceteareth-20, Ethylhexyl Methoxycrylene, Acrylates Copolymer, Polysorbate 60, Sorbitan Stearate, Caprylyl Glycol, Cetearyl Olivate, Panthenol, Sorbitan Olivate, Acrylates/C10-30 Alkyl Acrylate Crosspolymer, Ethylhexylglycerin, Tromethamine, Sodium Acrylate/Sodium Acryloyldimethyl Taurate Copolymer, 1,2-Hexanediol, Isohexadecane, Ammonium Acryloyldimethyltaurate/Vp Copolymer, Musa Sapientum Flower Extract, Rosa Damascena Flower Water, Pyrus Communis (Pear) Fruit Extract, Bht, Prunus Domestica Fruit Extract, Polysorbate 80, Cucumis Melo (Melon) Fruit Extract, Trisodium Ethylenediamine Disuccinate, Hedera Helix (Ivy) Leaf/Stem Extract, Xanthan Gum, Butylene Glycol, Glucosylrutin, Equisetum Arvense Extract, Lycopodium Clavatum Extract, Sodium Hyaluronate, Polyglutamic Acid, Hyaluronic Acid, Hydrolyzed Hyaluronic Acid, Hydrolyzed Sodium Hyaluronate, Hydroxypropyltrimonium Hyaluronate, Potassium Hyaluronate, Sodium Hyaluronate Crosspolymer, Betula Platyphylla Japonica Juice, Pentylene Glycol